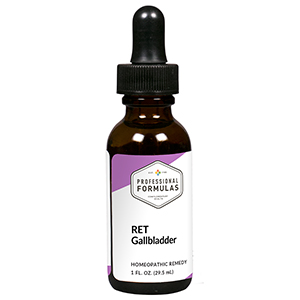 DRUG LABEL: RET Gallbladder
NDC: 63083-7007 | Form: LIQUID
Manufacturer: Professional Complementary Health Formulas
Category: homeopathic | Type: HUMAN OTC DRUG LABEL
Date: 20190815

ACTIVE INGREDIENTS: ULEX EUROPAEUS FLOWER 3 [hp_X]/29.5 mL; ELEUTHEROCOCCUS SENTICOSUS ROOT OIL 3 [hp_X]/29.5 mL; SALIX ALBA FLOWERING TOP 3 [hp_X]/29.5 mL; POTASSIUM PHOSPHATE, UNSPECIFIED FORM 3 [hp_X]/29.5 mL; COPPER 30 [hp_X]/29.5 mL; LACHESIS MUTA VENOM 30 [hp_X]/29.5 mL; LYCOPODIUM CLAVATUM SPORE 30 [hp_X]/29.5 mL; SODIUM CHLORIDE 30 [hp_X]/29.5 mL; DATURA STRAMONIUM 30 [hp_X]/29.5 mL
INACTIVE INGREDIENTS: ALCOHOL; WATER

RET7

ACTIVE INGREDIENTS

Gorse flower essence 3X
Rock water flower essence 3X
Willow flower essence 3X
Kali phosphoricum 3X, 6X, 30X
and all the following at 30X, 100X, 200X:
Cuprum metallicum
Lachesis mutus
Lycopodium clavatum
Natrum muriaticum
Stramonium

QUESTIONS

Professional Formulas

PO Box 2034 Lake Oswego, OR 97035

INDICATIONS

Temporarily relieves resentment, bitterness, self-pity, hopelessness, pessimism, self-perfection, dread, or anxiousness.*

PURPOSE

*Claims based on traditional homeopathic practice, not accepted medical evidence. Not FDA evaluated.

WARNINGS

In case of overdose, get medical help or contact a poison control center right away.

Keep out of the reach of children.

PREGNANCY OR BREAST FEEDING

If pregnant or breastfeeding, ask a healthcare professional before use.

DIRECTIONS

Place drops under tongue 30 minutes before/after meals. Adults and children 12 years and over: Take 5 drops up to 4 times per day for up to one month. Consult a physician for use in children under 12 years of age.

OTHER INFORMATION

Tamper resistant. If seal is broken, do not use. After opening, close container tightly and store at room temperature away from heat.

INACTIVE INGREDIENTS

20% ethanol, purified water.

LABEL

Est 1985

Professional Formulas

Complementary Health

RET Gallbladder

Homeopathic Remedy

1 FL. OZ. (29.5 mL)